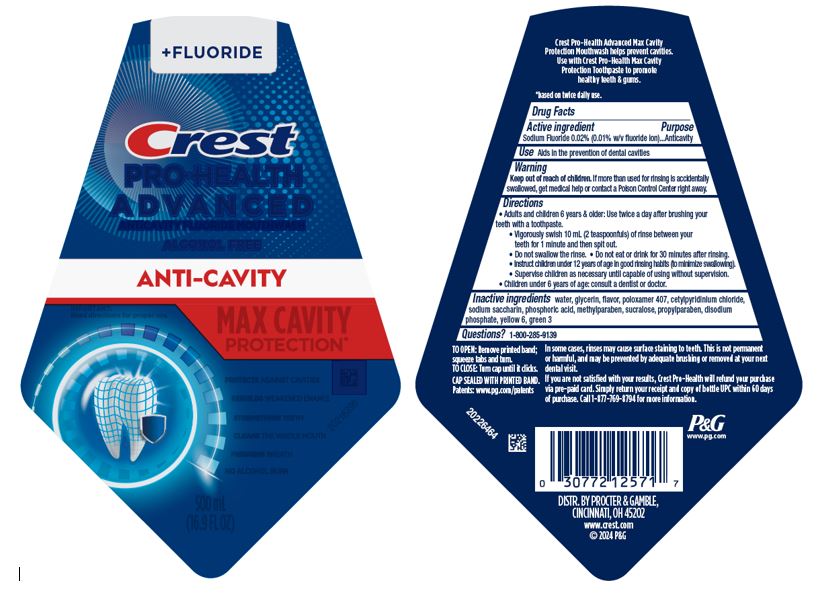 DRUG LABEL: Crest Pro-Health Advanced
NDC: 69423-848 | Form: RINSE
Manufacturer: The Procter & Gamble Manufacturing Company
Category: otc | Type: HUMAN OTC DRUG LABEL
Date: 20260106

ACTIVE INGREDIENTS: SODIUM FLUORIDE 2.2 mg/10 mL
INACTIVE INGREDIENTS: GLYCERIN; WATER; POLOXAMER 407; CETYLPYRIDINIUM CHLORIDE; SACCHARIN SODIUM; PHOSPHORIC ACID; METHYLPARABEN; SUCRALOSE; PROPYLPARABEN; SODIUM PHOSPHATE, DIBASIC, ANHYDROUS; FD&C YELLOW NO. 6; FD&C GREEN NO. 3

Crest®
Pro-Health Advanced
Anti-Cavity
Max Cavity Protection

Drug Facts

Active ingredient

Sodium Fluoride 0.02% (0.01% w/v fluoride ion)

Purpose

Anticavity

Use

Aids in the prevention of dental cavities

Warnings

Keep out of reach of children.If more than used for rinsing is accidentally swallowed, get medical help or contact a Poison Control Center right away.

Directions

- Adults and children 6 years & older:
  Use twice a day after brushing your teeth with a toothpaste.
- Vigorously swish 10 mL (2 teaspoonfuls) of rinse between your teeth for 1 minute and then spit out.
- Do not swallow the rinse.
- Do not eat or drink for 30 minutes after rinsing.
- Instruct children under 12 years of age in good rinsing habits (to minimize swallowing).
- Supervise children as necessary until capable of using without supervision.
- Children under 6 years of age: Consult a dentist or doctor.

Inactive ingredients

water, glycerin, flavor, poloxamer 407, cetylpyridinium chloride, sodium saccharin, phosphoric acid, methylparaben, sucralose, propylparaben, disodium phosphate, yellow 6, green 3

Questions?

1–800–285–9139

DISTR. BY PROCTER & GAMBLE,

CINCINNATI, OH 45202

PRINCIPAL DISPLAY PANEL - 500 mL Bottle Label

+ FLUORIDE

Crest

PRO-HEALTH

ADVANCED

ANTICAVITY FLUORIDE MOUTHWASH

ALCOHOL FREE

ANTI-CAVITY

IMPORTANT:

Read directions for proper use

MAX CAVITY

PROTECTION

PROTECTS AGAINST CAVITIES

REBUILDS WEAKENED ENAMEL

STRENGTHENS TEETH

CLEANS THE WHOLE MOUTH

FRESHENS BREATH

NO ALCOHOL BURN

500 mL

(16.9 fl oz)